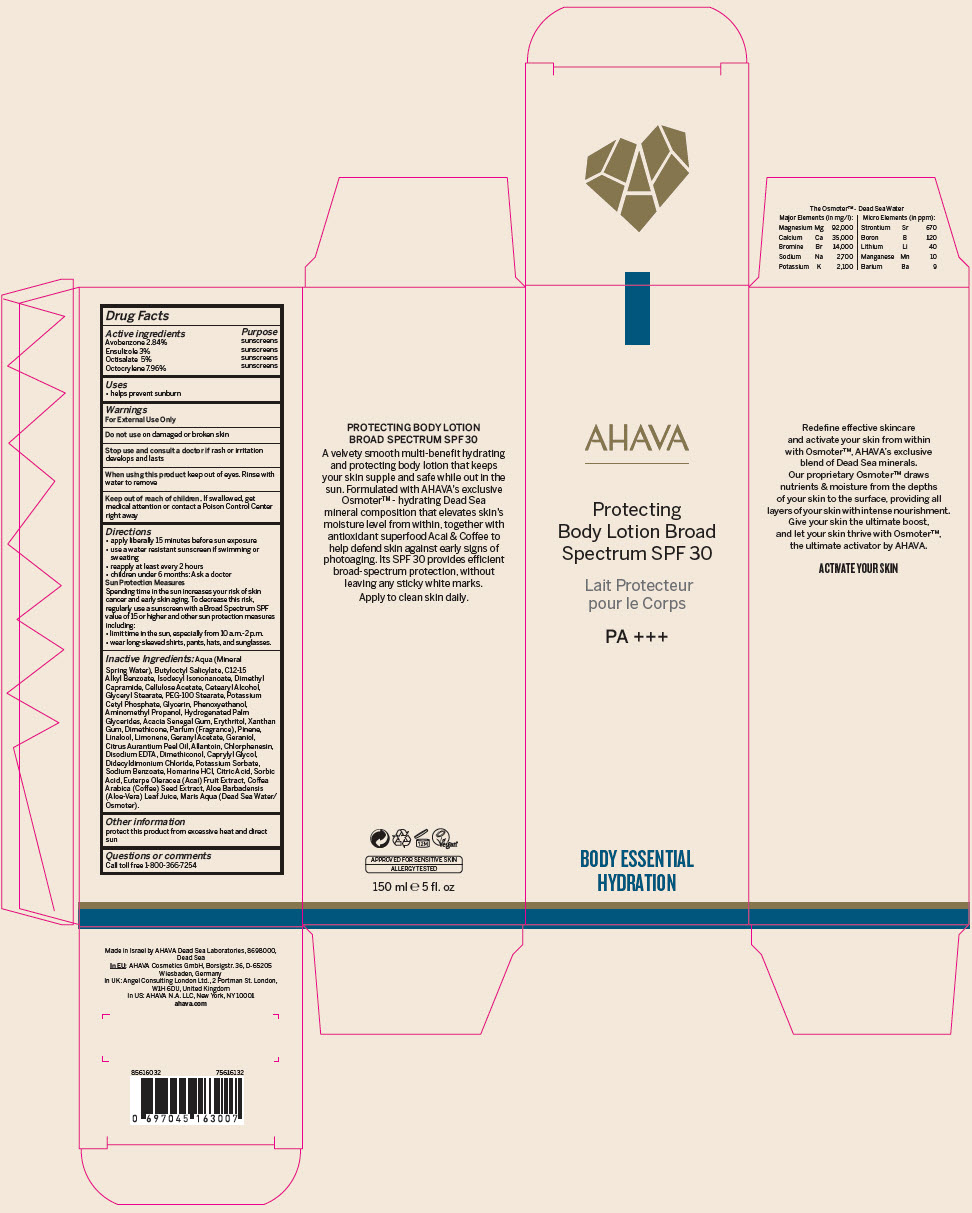 DRUG LABEL: AHAVA Protecting Body Broad Spectrum SPF 30
NDC: 60289-306 | Form: LOTION
Manufacturer: AHAVA - Dead Sea Laboratories Ltd
Category: otc | Type: HUMAN OTC DRUG LABEL
Date: 20241217

ACTIVE INGREDIENTS: Avobenzone 0.0284 g/1 mL; Ensulizole 0.03 g/1 mL; Octisalate 0.05 g/1 mL; Octocrylene 0.0796 g/1 mL
INACTIVE INGREDIENTS: Water; Butyloctyl Salicylate; Alkyl (C12-15) Benzoate; Isodecyl Isononanoate; Dimethyl Capramide; Cellulose Acetate; Cetostearyl Alcohol; Glyceryl Monostearate; PEG-100 Stearate; Potassium Cetyl Phosphate; Glycerin; Phenoxyethanol; Aminomethylpropanol; Hydrogenated Palm Glycerides; Acacia; Erythritol; Xanthan Gum; DIMETHICONE; Pinene; Linalool, (+/-)-; Limonene, (+)-; Geranyl Acetate; Geraniol; Bitter Orange Oil; Allantoin; Chlorphenesin; Edetate Disodium; Caprylyl Glycol; Didecyldimonium Chloride; Potassium Sorbate; Sodium Benzoate; Homarine Hydrochloride; Citric Acid Monohydrate; Sorbic Acid; Acai; Arabica Coffee Bean; Aloe Vera Leaf

AHAVA Protecting Body Lotion Broad Spectrum SPF 30

Drug Facts

ACTIVE INGREDIENT

Active ingredients | Purpose
Avobenzone 2.84% | sunscreens
Ensulizole 3% | sunscreens
Octisalate 5% | sunscreens
Octocrylene 7.96% | sunscreens

Uses

- helps prevent sunburn

Warnings

For External Use Only

Do not use on damaged or broken skin

Stop use and consult a doctor if rash or irritation develops and lasts

When using this product keep out of eyes. Rinse with water to remove

Keep out of reach of children. If swallowed, get medical attention or contact a Poison Control Center right away

Directions

- apply liberally 15 minutes before sun exposure
- use a water resistant sunscreen if swimming or sweating
- reapply at least every 2 hours
- children under 6 months: Ask a doctor

Sun Protection Measures

Spending time in the sun increases your risk of skin cancer and early skin aging. To decrease this risk, regularly use a sunscreen with a Broad Spectrum SPF value of 15 or higher and other sun protection measures including:

- limit time in the sun, especially from 10 a.m.-2 p.m.
- wear long-sleeved shirts, pants, hats, and sunglasses.

Inactive Ingredients

Aqua (Mineral Spring Water), Butyloctyl Salicylate, C12-15 Alkyl Benzoate, Isodecyl Isononanoate, Dimethyl Capramide, Cellulose Acetate, Cetearyl Alcohol, Glyceryl Stearate, PEG-100 Stearate, Potassium Cetyl Phosphate, Glycerin, Phenoxyethanol, Aminomethyl Propanol, Hydrogenated Palm Glycerides, Acacia Senegal Gum, Erythritol, Xanthan Gum, Dimethicone, Parfum (Fragrance), Pinene, Linalool, Limonene, Geranyl Acetate, Geraniol, Citrus Aurantium Peel Oil, Allantoin, Chlorphenesin, Disodium EDTA, Dimethiconol, Caprylyl Glycol, Didecyldimonium Chloride, Potassium Sorbate, Sodium Benzoate, Homarine HCl, Citric Acid, Sorbic Acid, Euterpe Oleracea (Acai) Fruit Extract, Coffea Arabica (Coffee) Seed Extract, Aloe Barbadensis (Aloe-Vera) Leaf Juice, Maris Aqua (Dead Sea Water/ Osmoter).

Other information

protect this product from excessive heat and direct sun

Questions or comments

Call toll free 1-800-366-7254

PRINCIPAL DISPLAY PANEL - 150 ml Tube Carton

AHAVA

Protecting
Body Lotion Broad
Spectrum SPF 30

PA +++

BODY ESSENTIAL
HYDRATION